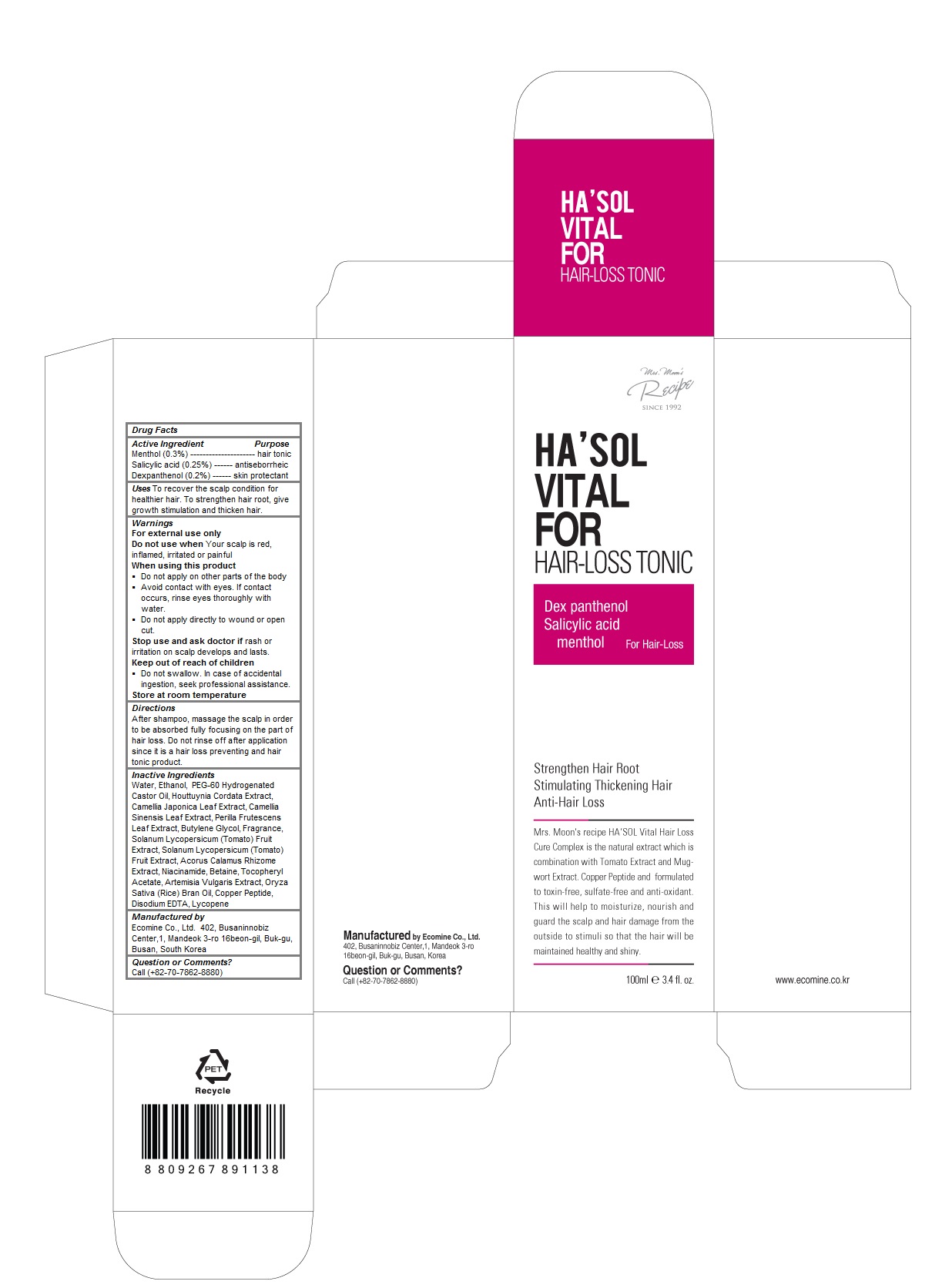 DRUG LABEL: HASOL Vital For Hair-Loss Tonic
NDC: 51270-125 | Form: LIQUID
Manufacturer: ECOMINE Co., Ltd.
Category: otc | Type: HUMAN OTC DRUG LABEL
Date: 20160402

ACTIVE INGREDIENTS: Dexpanthenol 0.002 1/100 mL; MENTHOL 0.003 1/100 mL; Salicylic Acid 0.0025 1/100 mL
INACTIVE INGREDIENTS: water; ALCOHOL; PEG-60 HYDROGENATED CASTOR OIL; HOUTTUYNIA CORDATA FLOWERING TOP; CAMELLIA JAPONICA LEAF; GREEN TEA LEAF; PERILLA FRUTESCENS TOP; Butylene Glycol; TOMATO; ACORUS CALAMUS ROOT; NIACINAMIDE; Betaine; .ALPHA.-TOCOPHEROL ACETATE; ARTEMISIA VULGARIS ROOT; RICE BRAN OIL; PREZATIDE COPPER; EDETATE DISODIUM; LYCOPENE

HA'SOL Vital For Hair-Loss Tonic